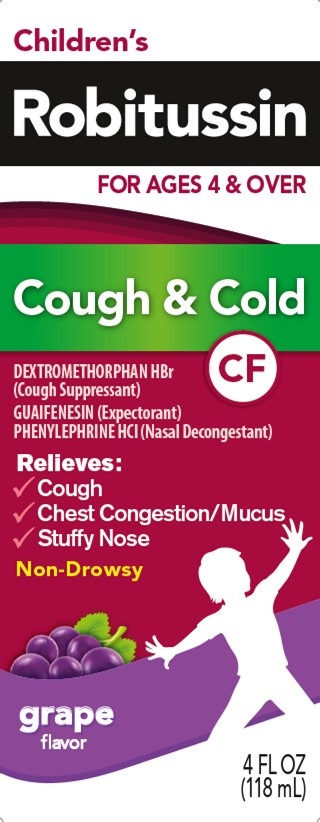 DRUG LABEL: Childrens Robitussin Cough and Cold CF
NDC: 0031-8716 | Form: LIQUID
Manufacturer: Haleon US Holdings LLC
Category: otc | Type: HUMAN OTC DRUG LABEL
Date: 20240317

ACTIVE INGREDIENTS: DEXTROMETHORPHAN HYDROBROMIDE 5 mg/5 mL; GUAIFENESIN 50 mg/5 mL; PHENYLEPHRINE HYDROCHLORIDE 2.5 mg/5 mL
INACTIVE INGREDIENTS: ANHYDROUS CITRIC ACID; FD&C RED NO. 40; GLYCERIN; PROPYLENE GLYCOL, (R)-; WATER; SODIUM BENZOATE; SODIUM CITRATE, UNSPECIFIED FORM; SORBITOL; SUCRALOSE

Drug Facts

Active ingredients (in each 10 mL)

Dextromethorphan HBr, USP 10 mg

Guaifenesin, USP 100 mg

Phenylephrine HCl, USP 5 mg

Purposes

Cough suppressant

Expectorant

Nasal decongestant

Uses

- helps loosen phlegm (mucus) and thin bronchial secretions to drain bronchial tubes
- temporarily relieves these symptoms occurring with a cold:
- nasal congestion
- cough due to minor throat and bronchial irritation

Warnings

DO NOT USE

Do not useif you are now taking a prescription monoamine oxidase inhibitor (MAOI) (certain drugs for depression, psychiatric, or emotional conditions, or Parkinson's disease), or for 2 weeks after stopping the MAOI drug. If you do not know if your prescription drug contains an MAOI, ask a doctor or pharmacist before taking this product.

Ask a doctor before use if you have

1. heart disease
2. high blood pressure
3. thyroid disease
4. diabetes
5. trouble urinating due to an enlarged prostate gland
6. cough that occurs with too much phlegm (mucus)
7. cough that lasts or is chronic such as occurs with smoking, asthma, chronic bronchitis or emphysema

Ask a doctor or pharmacist before use if you aretaking any other oral nasal decongestant or stimulant.

When using this product do not use more than directed.

Stop use and ask a doctor if

- you get nervous, dizzy, or sleepless
- symptoms do not get better within 7 days or are accompanied by fever
- cough lasts more than 7 days, comes back, or is accompanied by fever, rash, or persistent headache. These could be signs of a serious condition.

PREGNANCY OR BREAST FEEDING

If pregnant or breast-feeding,ask a health professional before use.

Keep out of reach of children.In case of overdose, get medical help or contact a Poison Control Center right away.

Directions

- measure only with dosing cup provided
- keep dosing cup with product
- mL = milliliter
- do not take more than 6 doses in any 24-hour period

age | dose
children under 4 years | do not use
children 4 to under 6 years | 5 mL every 4 hours
children 6 to under 12 years | 10 mL every 4 hours
adults and children 12 years and over | 20 mL every 4 hours

Other information

- each 10 mL contains:sodium 7 mg
- store at 20-25°C (68-77°F). Do not refrigerate.

Inactive ingredients

anhydrous citric acid, artificial flavor, FD&C red no. 40, glycerin, propylene glycol, purified water, sodium benzoate, sodium citrate, sorbitol solution, sucralose

Questions or comments?

call weekdays from 9 AM to 5 PM EST at 1-800-245-1040

Additional Information

Packaged with Tamper-Evident bottle cap. Do Not Use

if breakable ring is separated or missing.

Children’s

Robitussin liquid

is specially

Children’s Robitussin liquid is especially formulated to provide soothing action, control your child’s cough plus relieve other cold symptoms.

Should be 18 or older to purchase

PARENTS:

Learn about teen medicine abuse

www.StopMedicineAbuse.org

Distributed by: GSK Consumer Healthcare,

Warren, NJ 07059

For most recent product information,

visit www.robitussin.com

Trademarks owned or licensed by GSK.

©2022 GSK or licensor

Made in Canada

PRINCIPAL DISPLAY PANEL

Children's

Robitussin

FOR AGES 4 & OVER

Cough & Cold

CF

DEXTROMETHORPHAN HBr
(Cough Suppressant)
GUAIFENESIN (Expectorant)
PHENYLEPHRINE HCl (Nasal Decongestant)

Relieves:

- Cough
- Chest Congestion/Mucus
- Stuffy Nose

Non-Drowsy

grape
flavor

4 FL OZ
(118 mL)

PAA172104 Front Carton